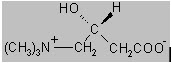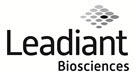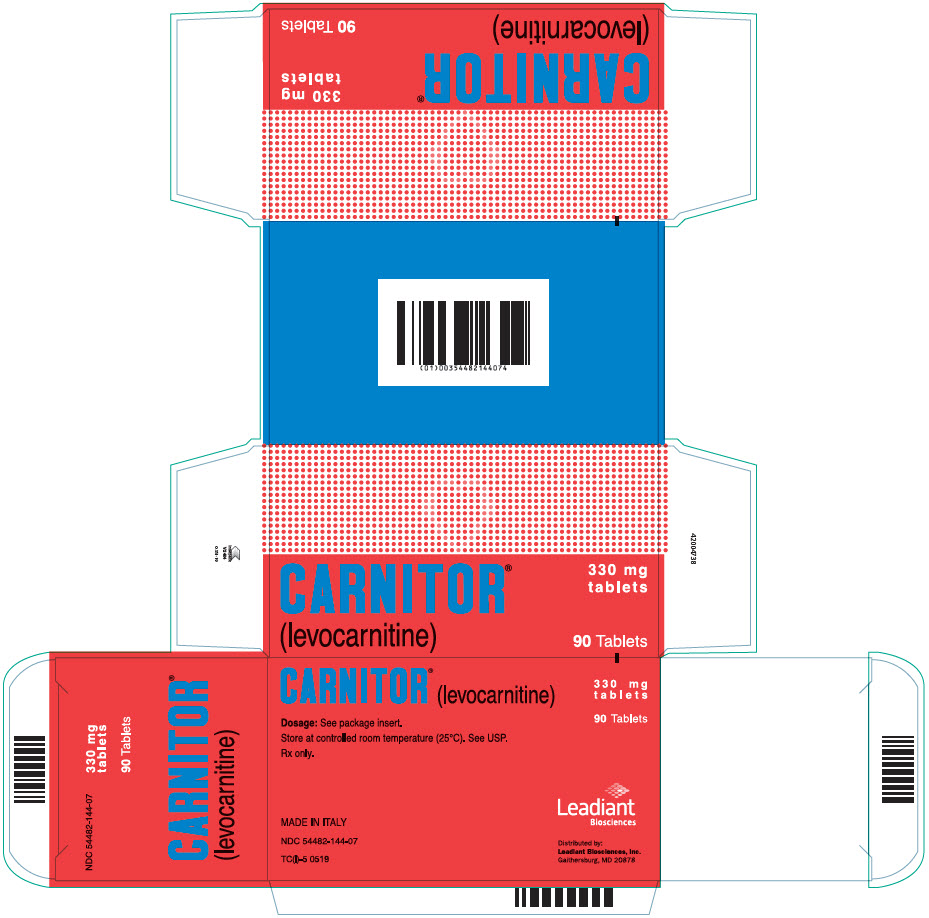 DRUG LABEL: CARNITOR
NDC: 54482-144 | Form: TABLET
Manufacturer: Leadiant Biosciences, Inc.
Category: prescription | Type: HUMAN PRESCRIPTION DRUG LABEL
Date: 20241030

ACTIVE INGREDIENTS: LEVOCARNITINE 330 mg/1 1
INACTIVE INGREDIENTS: MAGNESIUM STEARATE; MICROCRYSTALLINE CELLULOSE; POVIDONE, UNSPECIFIED

CARNITOR ® (levocarnitine) Tablets (330 mg)

For oral use only. Not for parenteral use.

DESCRIPTION

CARNITOR® (levocarnitine) is a carrier molecule in the transport of long-chain fatty acids across the inner mitochondrial membrane.

The chemical name of levocarnitine is 3-carboxy-2(R)-hydroxy-N,N,N-trimethyl-1-propanaminium, inner salt. Levocarnitine is a white crystalline, hygroscopic powder. It is readily soluble in water, hot alcohol, and insoluble in acetone. The specific rotation of levocarnitine is between -29° and -32°. Its chemical structure is:

Empirical Formula: C7H15NO3

Molecular Weight: 161.20

Each CARNITOR® (levocarnitine) Tablet contains 330 mg of levocarnitine and the inactive ingredients magnesium stearate, microcrystalline cellulose and povidone.

Each 118 mL container of CARNITOR® (levocarnitine) Oral Solution contains 1 g of levocarnitine/10 mL. Also contains: Artificial Cherry Flavor, D,L,-Malic Acid, Purified Water, Sucrose. Methylparaben NF and Propylparaben NF are added as preservatives. The pH is approximately 5.

Each 118 mL container of CARNITOR® SF (levocarnitine) Sugar-Free Oral Solution contains 1 g of levocarnitine/10 mL. Also contains: Natural Cherry Flavor, D,L,-Malic Acid, Purified Water, Sodium Saccharin USP. Methylparaben NF and Propylparaben NF are added as preservatives. The pH is approximately 5.

CLINICAL PHARMACOLOGY

CARNITOR® (levocarnitine) is a naturally occurring substance required in mammalian energy metabolism. It has been shown to facilitate long-chain fatty acid entry into cellular mitochondria, thereby delivering substrate for oxidation and subsequent energy production. Fatty acids are utilized as an energy substrate in all tissues except the brain. In skeletal and cardiac muscle, fatty acids are the main substrate for energy production.

Primary systemic carnitine deficiency is characterized by low concentrations of levocarnitine in plasma, RBC, and/or tissues. It has not been possible to determine which symptoms are due to carnitine deficiency and which are due to an underlying organic acidemia, as symptoms of both abnormalities may be expected to improve with CARNITOR®. The literature reports that carnitine can promote the excretion of excess organic or fatty acids in patients with defects in fatty acid metabolism and/or specific organic acidopathies that bioaccumulate acylCoA esters.^1-6

Secondary carnitine deficiency can be a consequence of inborn errors of metabolism. CARNITOR® may alleviate the metabolic abnormalities of patients with inborn errors that result in accumulation of toxic organic acids. Conditions for which this effect has been demonstrated are: glutaric aciduria II, methyl malonic aciduria, propionic acidemia, and medium chain fatty acylCoA dehydrogenase deficiency.^7,8 Autointoxication occurs in these patients due to the accumulation of acylCoA compounds that disrupt intermediary metabolism. The subsequent hydrolysis of the acylCoA compound to its free acid results in acidosis which can be life-threatening. Levocarnitine clears the acylCoA compound by formation of acylcarnitine, which is quickly excreted. Carnitine deficiency is defined biochemically as abnormally low plasma concentrations of free carnitine, less than 20 µmol/L at one week post term and may be associated with low tissue and/or urine concentrations. Further, this condition may be associated with a plasma concentration ratio of acylcarnitine/levocarnitine greater than 0.4 or abnormally elevated concentrations of acylcarnitine in the urine. In premature infants and newborns, secondary deficiency is defined as plasma levocarnitine concentrations below age-related normal concentrations.

PHARMACOKINETICS

In a relative bioavailability study in 15 healthy adult male volunteers, CARNITOR® Tablets were found to be bio-equivalent to CARNITOR® Oral Solution. Following 4 days of dosing with 6 tablets of CARNITOR® 330 mg b.i.d. or 2 g of CARNITOR® oral solution b.i.d., the maximum plasma concentration (Cmax) was about 80 µmol/L and the time to maximum plasma concentration (Tmax) occurred at 3.3 hours.

The plasma concentration profiles of levocarnitine after a slow 3 minute intravenous bolus dose of 20 mg/kg of CARNITOR® were described by a two-compartment model. Following a single i.v. administration, approximately 76% of the levocarnitine dose was excreted in the urine during the 0-24h interval. Using plasma concentrations uncorrected for endogenous levocarnitine, the mean distribution half life was 0.585 hours and the mean apparent terminal elimination half life was 17.4 hours.

The absolute bioavailability of levocarnitine from the two oral formulations of CARNITOR®, calculated after correction for circulating endogenous plasma concentrations of levocarnitine, was 15.1 ± 5.3% for CARNITOR® Tablets and 15.9 ± 4.9% for CARNITOR® Oral Solution.

Total body clearance of levocarnitine (Dose/AUC including endogenous baseline concentrations) was a mean of 4.00 L/h.

Levocarnitine was not bound to plasma protein or albumin when tested at any concentration or with any species including the human.^9

METABOLISM AND EXCRETION

In a pharmacokinetic study where five normal adult male volunteers received an oral dose of [^3H-methyl]-L-carnitine following 15 days of a high carnitine diet and additional carnitine supplement, 58 to 65% of the administered radioactive dose was recovered in the urine and feces in 5 to 11 days. Maximum concentration of [^3H-methyl]-L-carnitine in serum occurred from 2.0 to 4.5 hr after drug administration. Major metabolites found were trimethylamine N-oxide, primarily in urine (8% to 49% of the administered dose) and [^3H]-γ-butyrobetaine, primarily in feces (0.44% to 45% of the administered dose). Urinary excretion of levocarnitine was about 4 to 8% of the dose. Fecal excretion of total carnitine was less than 1% of the administered dose.^10

After attainment of steady state following 4 days of oral administration of CARNITOR® Tablets (1980 mg q12h) or Oral Solution (2000 mg q12h) to 15 healthy male volunteers, the mean urinary excretion of levocarnitine during a single dosing interval (12h) was about 9% of the orally administered dose (uncorrected for endogenous urinary excretion).

INDICATIONS AND USAGE

CARNITOR® (levocarnitine) is indicated in the treatment of primary systemic carnitine deficiency. In the reported cases, the clinical presentation consisted of recurrent episodes of Reye-like encephalopathy, hypoketotic hypoglycemia, and/or cardiomyopathy. Associated symptoms included hypotonia, muscle weakness and failure to thrive. A diagnosis of primary carnitine deficiency requires that serum, red cell and/or tissue carnitine levels be low and that the patient does not have a primary defect in fatty acid or organic acid oxidation (see CLINICAL PHARMACOLOGY). In some patients, particularly those presenting with cardiomyopathy, carnitine supplementation rapidly alleviated signs and symptoms. Treatment should include, in addition to carnitine, supportive and other therapy as indicated by the condition of the patient.

CARNITOR® (levocarnitine) is also indicated for acute and chronic treatment of patients with an inborn error of metabolism which results in a secondary carnitine deficiency.

CONTRAINDICATIONS

None known.

WARNINGS

Hypersensitivity Reactions

Serious hypersensitivity reactions, including rash, urticaria, and facial edema have been reported with oral CARNITOR®. Other serious hypersensitivity reactions, including anaphylaxis, laryngeal edema, and bronchospasm have been reported following intravenous levocarnitine administration, mostly in patients with end stage renal disease undergoing dialysis.

Discontinue use of CARNITOR® and instruct patients to seek medical attention if they experience symptoms suggestive of a hypersensitivity reaction.

PRECAUTIONS

General

CARNITOR® (levocarnitine) Oral Solution and CARNITOR® SF (levocarnitine) Sugar-Free Oral Solution are for oral/internal use only.

Not for parenteral use.

Gastrointestinal reactions may result from a too rapid consumption of carnitine. CARNITOR® (levocarnitine) Oral Solution and CARNITOR® SF (levocarnitine) Sugar-Free Oral Solution may be consumed alone, or dissolved in drinks or other liquid foods to reduce taste fatigue. They should be consumed slowly and doses should be spaced evenly throughout the day to maximize tolerance.

The safety and efficacy of oral levocarnitine has not been evaluated in patients with renal insufficiency. Chronic administration of high doses of oral levocarnitine in patients with severely compromised renal function or in ESRD patients on dialysis may result in accumulation of the potentially toxic metabolites, trimethylamine (TMA) and trimethylamine-N-oxide (TMAO), since these metabolites are normally excreted in the urine.

Drug Interactions

Reports of INR increase with the use of warfarin have been observed. It is recommended that INR levels be monitored in patients on warfarin therapy after the initiation of treatment with levocarnitine or after dose adjustments.

Carcinogenesis, Mutagenesis, Impairment of Fertility

Mutagenicity tests performed in Salmonella typhimurium, Saccharomyces cerevisiae, and Schizosaccharomyces pombe indicate that levocarnitine is not mutagenic. No long-term animal studies have been performed to evaluate the carcinogenic potential of levocarnitine.

Pregnancy

Reproductive studies have been performed in rats and rabbits at doses up to 3.8 times the human dose on the basis of surface area and have revealed no evidence of impaired fertility or harm to the fetus due to CARNITOR®. There are, however, no adequate and well controlled studies in pregnant women.

Because animal reproduction studies are not always predictive of human response, this drug should be used during pregnancy only if clearly needed.

Nursing Mothers

Levocarnitine supplementation in nursing mothers has not been specifically studied.

Studies in dairy cows indicate that the concentration of levocarnitine in milk is increased following exogenous administration of levocarnitine. In nursing mothers receiving levocarnitine, any risks to the child of excess carnitine intake need to be weighed against the benefits of levocarnitine supplementation to the mother. Consideration may be given to discontinuation of nursing or of levocarnitine treatment.

Pediatric Use

See DOSAGE AND ADMINISTRATION.

ADVERSE REACTIONS

The following adverse reactions associated with the use of oral formulations of levocarnitine were identified in clinical trials or postmarketing reports. Because these reactions were reported voluntarily from a population of uncertain size, it is not always possible to estimate their frequency, reliability, or to establish a causal relationship to drug exposure.

Gastrointestinal Reactions: Various mild gastrointestinal complaints have been reported during the long-term administration of oral L- or D,L-carnitine; these include transient nausea and vomiting, abdominal cramps, and diarrhea. Gastrointestinal adverse reactions with CARNITOR® (levocarnitine) Oral Solution or CARNITOR® SF (levocarnitine) Sugar-Free Oral Solution dissolved in liquids might be avoided by a slow consumption of the solution or by a greater dilution. Decreasing the dosage often diminishes or eliminates drug-related patient body odor or gastrointestinal symptoms when present. Tolerance should be monitored very closely during the first week of administration, and after any dosage increases.

Musculoskeletal Reactions: Mild myasthenia has been described only in uremic patients receiving D,L-carnitine.

Neurologic Reactions: Seizures have been reported to occur in patients with or without pre-existing seizure activity receiving either oral or intravenous levocarnitine. In patients with pre-existing seizure activity, an increase in seizure frequency and/or severity has been reported.

Hypersensitivity Reactions: Rash, urticaria, and facial edema have been reported with oral CARNITOR® (see WARNINGS).

OVERDOSAGE

There have been no reports of toxicity from levocarnitine overdosage. Levocarnitine is easily removed from plasma by dialysis. The intravenous LD50 of levocarnitine in rats is 5.4 g/kg and the oral LD50 of levocarnitine in mice is 19.2 g/kg. Large doses of levocarnitine may cause diarrhea.

DOSAGE AND ADMINISTRATION

CARNITOR® (levocarnitine) Tablets.

Adults: The recommended oral dosage for adults is 990 mg two or three times a day using the 330 mg tablets, depending on clinical response.

Infants and children: The recommended oral dosage for infants and children is between 50 and 100 mg/kg/day in divided doses, with a maximum of 3 g/day. Dosage should begin at 50 mg/kg/day. The exact dosage will depend on clinical response.

Monitoring should include periodic blood chemistries, vital signs, plasma carnitine concentrations and overall clinical condition.

CARNITOR® (levocarnitine) Oral Solution and CARNITOR® SF (levocarnitine) Sugar-Free Oral Solution.

For oral use only. Not for parenteral use.

Adults: The recommended dosage of levocarnitine is 1 to 3 g/day for a 50 kg subject, which is equivalent to 10 to 30 mL/day of CARNITOR® (levocarnitine) Oral Solution or CARNITOR® SF (levocarnitine) Sugar-Free Oral Solution. Higher doses should be administered only with caution and only where clinical and biochemical considerations make it seem likely that higher doses will be of benefit. Dosage should start at 1 g/day, (10 mL/day), and be increased slowly while assessing tolerance and therapeutic response. Monitoring should include periodic blood chemistries, vital signs, plasma carnitine concentrations, and overall clinical condition.

Infants and children: The recommended dosage of levocarnitine is 50 to 100 mg/kg/day which is equivalent to 0.5 mL/kg/day CARNITOR® (levocarnitine) Oral Solution or CARNITOR® SF (levocarnitine) Sugar-Free Oral Solution. Higher doses should be administered only with caution and only where clinical and biochemical considerations make it seem likely that higher doses will be of benefit. Dosage should start at 50 mg/kg/day, and be increased slowly to a maximum of 3 g/day (30 mL/day) while assessing tolerance and therapeutic response. Monitoring should include periodic blood chemistries, vital signs, plasma carnitine concentrations, and overall clinical condition.

CARNITOR® (levocarnitine) Oral Solution or CARNITOR® SF (levocarnitine) Sugar-Free Oral Solution may be consumed alone or dissolved in drink or other liquid food. Doses should be spaced evenly throughout the day (every three or four hours) preferably during or following meals and should be consumed slowly in order to maximize tolerance.

HOW SUPPLIED

CARNITOR® (levocarnitine) Tablets are supplied as 330 mg tablets embossed with "CARNITOR ST" in individual blisters, packaged in boxes of 90 (NDC 54482-144-07). Store in original packaging: content hygroscopic. Store at 20°C to 25°C (68°F to 77°F). See USP Controlled Room Temperature. CARNITOR® (levocarnitine) Tablets are distributed by Leadiant Biosciences, Inc.

CARNITOR® (levocarnitine) Oral Solution is supplied in 118 mL (4 FL. OZ.) plastic containers (NDC 54482-145-08 and NDC 54482-145-09). Store at 20°C to 25°C (68°F to 77°F). See USP Controlled Room Temperature. Avoid excessive heat and protect from freezing. CARNITOR® (levocarnitine) Oral Solution is distributed by Leadiant Biosciences, Inc.

CARNITOR® SF (levocarnitine) Sugar-Free Oral Solution is supplied in 118 mL (4 FL. OZ.) plastic containers (NDC 54482-148-01 and NDC 54482-148-02). Store at 20°C to 25°C (68°F to 77°F). See USP Controlled Room Temperature. Avoid excessive heat and protect from freezing. CARNITOR® SF (levocarnitine) Sugar-Free Oral Solution is distributed by Leadiant Biosciences, Inc.

Rx only.

REFERENCES

1. Bohmer, T., Rydning, A. and Solberg, H.E. 1974. Carnitine levels in human serum in health and disease. Clin. Chim. Acta 57:55-61.
2. Brooks, H., Goldberg, L., Holland, R. et al. 1977. Carnitine-induced effects on cardiac and peripheral hemodynamics. J. Clin. Pharmacol. 17:561-568.
3. Christiansen, R., Bremer, J. 1976. Active transport of butyrobetaine and carnitine into isolated liver cells. Biochim. Biophys. Acta 448:562-577.
4. Lindstedt, S. and Lindstedt, G. 1961. Distribution and excretion of carnitine in the rat. Acta Chem. Scand. 15:701-702.
5. Rebouche, C.J. and Engel, A.G. 1983. Carnitine metabolism and deficiency syndromes. Mayo Clin. Proc. 58:533-540.
6. Rebouche, C.J. and Paulson, D.J. 1986. Carnitine metabolism and function in humans. Ann. Rev. Nutr. 6:41-66.
7. Scriver, C.R., Beaudet, A.L., Sly, W.S. and Valle, D. 1989. The Metabolic Basis of Inherited Disease. New York: McGraw-Hill.
8. Schaub, J., Van Hoof, F. and Vis, H.L. 1991. Inborn Errors of Metabolism. New York: Raven Press.
9. Marzo, A., Arrigoni Martelli, E., Mancinelli, A., Cardace, G., Corbelletta, C., Bassani, E. and Solbiati, M. 1991. Protein binding of L-carnitine family components. Eur. J. Drug Met. Pharmacokin. Special Issue III: 364-368.
10. Rebouche, C.J. 1991. Quantitative estimation of absorption and degradation of a carnitine supplement by human adults. Metabolism 40:1305-1310.

PREVIOUS EDITION IS OBSOLETE
Date of Issue: 07/23
OPI-16

PRINCIPAL DISPLAY PANEL - 330 mg Tablet Blister Pack Carton

CARNITOR® (levocarnitine)

330 mg
tablets

90 Tablets

Dosage: See package insert.

Store at controlled room temperature (25°C). See USP.

Rx only.

MADE IN ITALY

NDC 54482-144-07

TC(I)-5 0519

Leadiant
Biosciences

Distributed by:
Leadiant Biosciences, Inc.
Gaithersburg, MD 20878